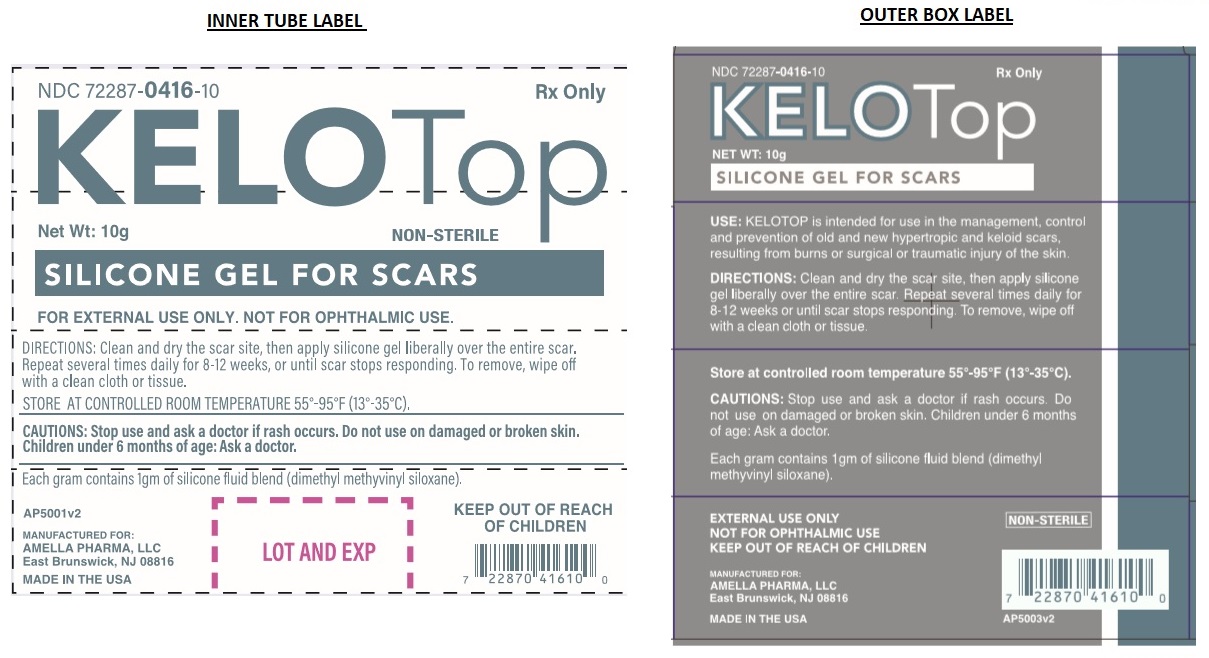 DRUG LABEL: Kelotop
NDC: 72287-416
Manufacturer: AMELLA PHARMA, LLC
Category: other | Type: MEDICAL DEVICE
Date: 20181228

KELOTop®

KELOTOP® SILICONE GEL – DIMETHYL METHYLVINYL SILOXANE– ELASTOMER, SILICONE, FOR SCAR MANAGEMENT

Rx Only

For external use only

Not for ophthalmic use

INDICATIONS

KELOTOP® Silicone Gel is intended for use in the management, control and prevention of old and new hypertrophic or keloid scars resulting from burns or surgical or traumatic injury of the skin, by forming an occlusive barrier.

CONTRAINDICATIONS

Do not use on open wounds or when any Dermatological conditions disrupt the skin (such as a rash and/or burns).

KELOTOP® Silicone Gel is contraindicated in patients with known hypersensitivity to silicone or any of the listed ingredients.

WARNINGS, PRECAUTIONS, ADVERSE REACTIONS

Possible complications include:
• Superficial maceration of the skin • Rash
• Skin Discoloration • Pruritus

Rashes have been observed on skin under the KELOTOP® Silicone Gel, this has been attributed to poor or insufficient cleansing of the scar area. Should a rash occur, stop using the KELOTOP® Silicone Gel for 12 hours followed by using the KELOTOP® Silicone Gel for 12 hours. If the rash persists, a physician should be contacted and KELOTOP® Silicone Gel use should be discontinued.

Discoloration of the skin covered by KELOTOP® Silicone Gel has been reported, particularly in dark skinned patients. This effect appears to be transient, and may be similar to the discoloration experienced whenever an area of skin is covered for extended periods of time.

If ingested, get medical help or contact Poison Control Center right away.

Do not use creams, lotions, sun block or other silicone products over and around the scar area when wearing KELOTOP® Silicone Gel. These products will create a barrier between the scar site and the silicone gel, preventing a proper healing environment.

Call your doctor about side effects. You may report side effects to FDA at 1-800-FDA-1088. KEEP OUT OF REACH OF CHILDREN.

Precautions:

1. Do not apply to an open wound or third degree burn.

2. Never use on a sutured wound until sutures have been removed.

3. In rare instances Silicone Gel may cause a rash on the skin. This condition may result from improper cleaning of the scar area. Should the skin irritation still occur, discontinue use and consult your physician.

4. It is not recommended that this product be used on children under six months of age.

INGREDIENTS

Each KELOTOP® Silicone Gel contains: Dimethyl Methylvinyl Siloxane.

INSTRUCTIONS FOR USE:

1. Wash both scar and hands per cleaning instructions. Ensure the scar site is dry prior to each application.
2. Apply KELOTOP® Silicone Gel liberally over the entire scar area. It is recommended that this procedure be repeated several times daily for 8-12 weeks or until scar stops responding.
3. KELOTOP® Silicone Gel once applied will have a “tacky” appearance and feel which is natural and to be expected.
4. To remove, wipe off with a clean cloth or tissue.

CLEANING INSTRUCTIONS Every 12 hours the scar area should be washed. First wipe KELOTOP® Silicone Gel off the scar area with a clean cloth or tissue. Then gently wash the scar area with soapy water, rinse, and then let air dry.

WEARING TIME Optimal wearing time for KELOTOP® Silicone Gel is 24 hours per day. If it is not possible to wear the KELOTOP® Silicone Gel for the recommended 24 hour period, a minimum of 12 hours per day is required, washing per the instructions above once in that period. Follow this procedure each day, washing and re-applying the KELOTOP® Silicone Gel several times daily. The overall optimal period of use is usually 8 to 12 weeks or until scar stops responding.

HOW IT IS SUPPLIED

KELOTOP® Silicone Gel are supplied as a clear gel. Non-sterile product is labeled as such and supplied in a protective package within a protective outer container.

KELOTOP® Silicone Gel is available as the following:

NDC 72287-416-10 10gm tube

Store at 55°-95°F (13°-35°C); Keep away from heat and protect from freezing. Do not refrigerate.

NON-STERILE

Manufactured for:
Amella Pharma, LLC
East Brunswick, NJ 08816

12/2018 AP-5002v1
KELOTOP® is a registered Trademark of Amella Pharma, LLC

MADE IN THE USA